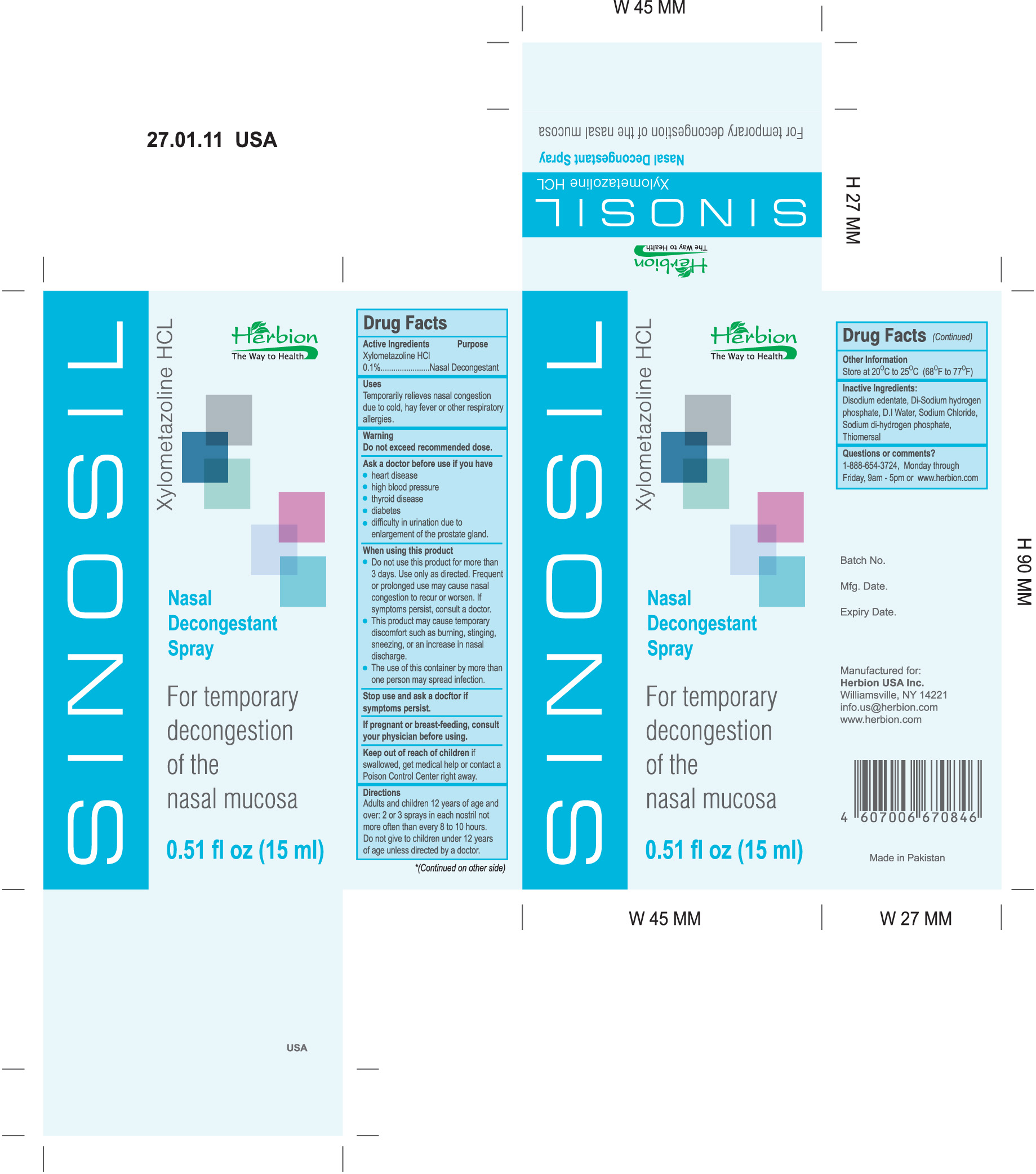 DRUG LABEL: Sinosil
NDC: 44237-007 | Form: SPRAY
Manufacturer: Herbion Pakistan Pvt Ltd
Category: otc | Type: HUMAN OTC DRUG LABEL
Date: 20110209

ACTIVE INGREDIENTS: XYLOMETAZOLINE HYDROCHLORIDE .015 mL/15 mL
INACTIVE INGREDIENTS: EDETATE DISODIUM; WATER; SODIUM CHLORIDE; THIMEROSAL

ACTIVE INGREDIENT

Xylometazoline HCl 0.1%

PURPOSE

Nasal Decongestant

INDICATIONS AND USAGE

Temporarily relieves nasal congestion due to cold, hay fever or other respiratory allergies.

WARNINGS

Do not exceed recommended dose.

Ask a doctor before use if you have

- heart disease
- high blood pressure
- thyroid disease
- diabetes
- difficulty in urination due to enlargement of the prostate gland

When using this product

- Do not use this product for more than 3 days. Use only as directed. Frequent or prolonged use may cause nasal congestion to recur or worsen. If symptoms persist, consult a doctor.
- This product may cause temporary discomfort such as burning, stinging, sneezing or an increase in nasal discharge.
- The use of this container by more than one person may spread infection.

Stop use and ask a doctor if symptoms persist.

PREGNANCY OR BREAST FEEDING

If pregnant or breast feeding, consult your physician before using.

Keep out of reach of children if swallowed, get medical help or contact a Poison Control Center right away.

DOSAGE AND ADMINISTRATION

Adults and children 12 years of age and over: 2 or 3 sprays in each nostril not more often than every 8 to 10 hours. Do not give to children under 12 years of age unless directed by a doctor.

STORAGE AND HANDLING

Store at 20-25 degrees C (68-77 degrees F)

INACTIVE INGREDIENT

Disodium edetate, Di-sodium hydrogen phosphate, D.I. Water, Sodium Chloride, Sodium di-hydrogen phosphate, thiomersal

Questions or comments?

1-888-654-3724, Monday through Friday, 9am-5pm or www.herbion.com

PACKAGE LABEL

Nasal Decongestant Spray

For temporary decongestion of the nasal mucosa